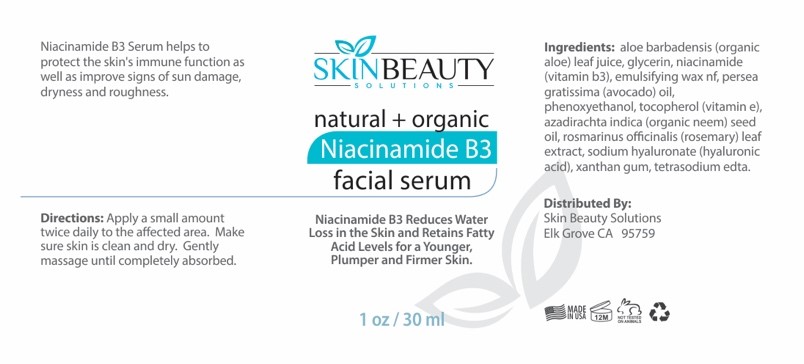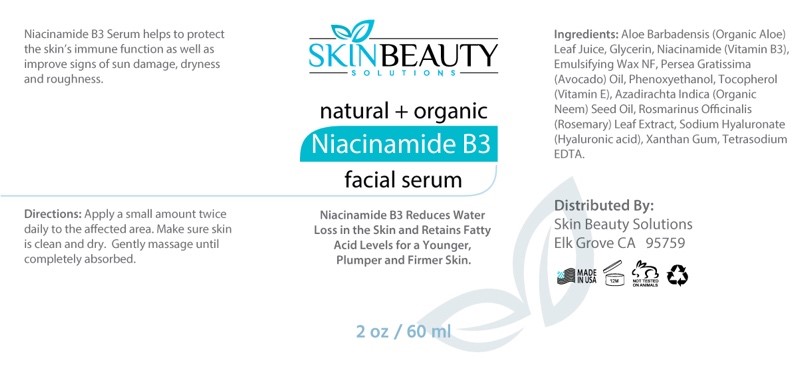 DRUG LABEL: Niacinamide B3 Serum
NDC: 84785-0006 | Form: SOLUTION
Manufacturer: Gazebo Wellness SKIN LLC
Category: otc | Type: HUMAN OTC DRUG LABEL
Date: 20241216

ACTIVE INGREDIENTS: ALOE VERA LEAF 0.3 mg/30 mL; ROSEMARY 0.3 mg/30 mL; HYALURONIC ACID 0.3 mg/30 mL; NIACINAMIDE 0.3 mg/30 mL; AVOCADO OIL 0.3 mg/30 mL
INACTIVE INGREDIENTS: TETRASODIUM EDETATE DIHYDRATE; PHENOXYETHANOL; VITAMIN E POLYETHYLENE GLYCOL SUCCINATE; GLYCERIN; XANTHAN GUM

DOSAGE AND ADMINISTRATION

Niacinamide 83 Serum helps to protect the skin's immune function as well as improve signs of sun damage, dryness and roughness.

WARNINGS

Directions: Apply a small amount twice daily to the affected area. Make sure skin is clean and dry. Gently massage until completely absorbed.

INACTIVE INGREDIENT

Inactive ingredients: Glycerin, Emulsifying Wax NF, Phenoxyethanol, Xanthan Gum, Tetrasodium EDTA.

ACTIVE INGREDIENT

Active ingredients: Aloe Vera Leaf Juice, Niacinamide (Vitamin B3), Avocado Oil, Vitamin E, Organic Neem Seed Oil, Rosemary Leaf Extract, Hyaluronic Acid.

INDICATIONS AND USAGE

Apply a small amount twice daily to the affected area. Make sure skin is clean and dry. Gently massage until completely absorbed.

keep out of reach of children

PURPOSE

natural + organic Niacinamide B3 facial serum
Niacinamide 83 Reduces Water Loss in the Skin and Retains Fatty Acid Levels for a Younger, Plumper and Firmer Skin.

Distributed By: Skin Beauty Solutions Elk Grove CA 95759

PACKAGE LABEL

Content of labeling